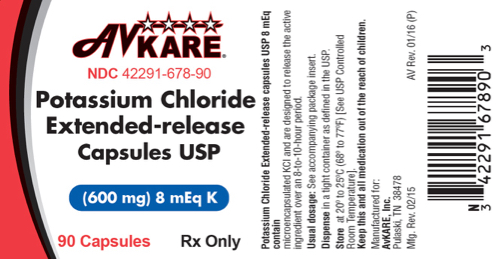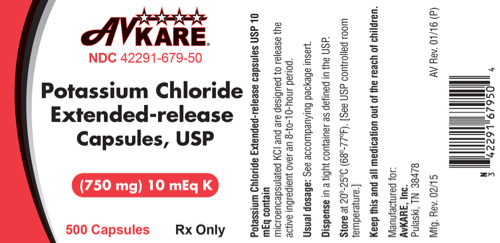 DRUG LABEL: Potassium Chloride
NDC: 42291-678 | Form: CAPSULE, EXTENDED RELEASE
Manufacturer: AvKARE
Category: prescription | Type: HUMAN PRESCRIPTION DRUG LABEL
Date: 20260115

ACTIVE INGREDIENTS: POTASSIUM CHLORIDE 600 mg/1 1
INACTIVE INGREDIENTS: ETHYLCELLULOSES; GELATIN; SODIUM LAURYL SULFATE; TITANIUM DIOXIDE; TRIACETIN

Potassium Chloride Extended-release Capsules, USP

Rx Only

DESCRIPTION:

Potassium Chloride Extended-release Capsules USP, 8 mEq and 10 mEq are oral dosage forms of

microencapsulated potassium chloride containing 600 mg and 750 mg of potassium chloride, USP

equivalent to 8 mEq and 10 mEq of potassium, respectively.

Dispersibility of potassium chloride (KCl) is accomplished by microencapsulation and a dispersing

agent. The resultant flow characteristics of the KCl microcapsules and the controlled release of K+

ions by the microcapsular membrane are intended to avoid the possibility that excessive amounts of KCl

can be localized at any point on the mucosa of the gastrointestinal tract.

Each crystal of KCl is microencapsulated by a process with an insoluble polymeric coating which

functions as a semi-permeable membrane; it allows for the controlled release of potassium and chloride

ions over an eight-to-ten-hour period. Fluids pass through the membrane and gradually dissolve the

potassium chloride within the micro-capsules. The resulting potassium chloride solution slowly

diffuses outward through the membrane. Potassium Chloride Extended-release Capsules, USP, 8 mEq

and 10 mEq are electrolyte replenishers.

The chemical name of the active ingredient is potassium chloride and the structural formula is KCl. It

has a molecular mass of 74.55. Potassium chloride, USP occurs as a white granular powder or as

colorless crystals. It is odorless and has a saline taste. Its solutions are neutral to litmus. It is freely

soluble in water and insoluble in alcohol.

The inactive ingredients are, ethylcellulose, FD&C blue #1, FD&C red # 40, gelatin, sodium lauryl

sulfate, titanium oxide and triacetin.

CLINICAL PHARMACOLOGY:

12.1 Mechanis m of Action

The potassium ion (K+) is the principal intracellular cation of most body tissues. Potassium ions

participate in a number of essential physiological processes, including the maintenance of intracellular

tonicity; the transmission of nerve impulses; the contraction of cardiac, skeletal, and smooth muscle; and

the maintenance of normal renal function.

The intracellular concentration of potassium is approximately 150 to 160 mEq per liter. The normal

adult plasma concentration is 3.5 to 5 mEq per liter. An active ion transport system maintains this gradient

across the plasma membrane.

Potassium is a normal dietary constituent and under steady-state conditions the amount of potassium

absorbed from the gastrointestinal tract is equal to the amount excreted in the urine. The usual dietary

intake of potassium is 50 to 100 mEq per day.

12.3 Pharmacokinetics

Each crystal of KCl is microencapsulated and allows for the controlled release of potassium and

chloride ions over an eight- to ten-hour period.

Specific Populations

Cirrhotics

Based on publish literature, the baseline corrected serum concentrations of potassium measured over 3

hours after administration in cirrhotic subjects who received an oral potassium load rose to

approximately twice that of normal subjects who received the same load.

INDICATIONS AND USAGE:

Potassium chloride extended-release capsules are indicated for the treatment and prophylaxis of

hypokalemia in adults and children with or without metabolic alkalosis, in patients for whom dietary

management with potassium-rich foods or diuretic dose reduction is insufficient.

CONTRAINDICATIONS:

Potassium chloride extended-release capsules are contraindicated in patients on amiloride or

triamterene.

WARNINGS:

Solid oral dosage forms of potassium chloride can produce ulcerative and/or stenotic lesions of the

gastrointestinal tract, particularly if the drug is in contact with the gastrointestinal mucosa for a

prolonged period of time. Consider the use of liquid potassium in patients with dysphagia, swallowing

disorders, or severe gastrointestinal motility disorders.

If severe vomiting, abdominal pain, distention, or gastrointestinal bleeding occurs, discontinue

potassium chloride extended-release capsules and consider possibility of ulceration, obstruction or

perforation.

Potassium chloride extended-release capsules should not be taken on an empty stomach because of its

potential for gastric irritation [see Dosage and Administration (2.1)].

PRECAUTIONS:

GENERAL PRECAUTIONS

General The diagnosis of potassium depletion is ordinarily made by demonstrating hypokalemia in a patient with a clinical history suggesting some cause for potassium depletion. In interpreting the serum potassium level, the physician should bear in mind that acute alkalosis per se can produce hypokalemia in the absence of a deficit in total body potassium, while acute acidosis per se can increase the serum potassium concentration into the normal range even in the presence of a reduced total body potassium. The treatment of potassium depletion, particularly in the presence of cardiac disease, renal disease, or acidosis, requires careful attention to acid-base balance and appropriate monitoring of serum electrolytes, the electrocardiogram, and the clinical status of the patient.

Information For Patients

Physicians should consider reminding the patient of the following: To take each dose with meals and with a full glass of water or other suitable liquid. To take each dose without crushing, chewing, or sucking the capsules. To take this medicine following the frequency and amount prescribed by the physician. This is especially important if the patient is also taking diuretics and/or digitalis preparations. To check with the physician if there is trouble swallowing capsules or if the capsules seem to stick in the throat.

To check with the physician at once if tarry stools or other evidence of gastrointestinal bleeding is noticed.

LABORATORY TESTS

Laboratory Tests Regular serum potassium determinations are recommended, especially in patients with renal insufficiency or diabetic nephropathy. When blood is drawn for analysis of plasma potassium it is important to recognize that artifactual elevations can occur after improper venipuncture technique or as a result of in vitro hemolysis of the sample.

DRUG INTERACTIONS

Drug Interactions Potassium-sparing diuretics, angiotensin converting enzyme inhibitors (see WARNINGS).

CARCINOGENESIS AND MUTAGENESIS AND IMPAIRMENT OF FERTILITY

Carcinogenesis, mutagenesis, impairment of fertility Carcinogenicity, mutagenicity and fertility studies in animals have not been performed. Potassium is a normal dietary constituent.

PREGNANCY

There are no human data related to use of potassium chloride extended-release capsules during

pregnancy and animal reproductive studies have not been conducted. Potassium supplementation that

does not lead to hyperkalemia is not expected to cause fetal harm.

The background risk for major birth defects and miscarriage in the indicated population is unknown. All

pregnancies have a background risk of birth defect, loss, or other adverse outcomes. In the U.S. general

population, the estimated background risk of major birth defects and miscarriage in clinically

recognized pregnancies is 2 to 4% and 15 to 20%, respectively.

NURSING MOTHERS

The normal potassium ion content of human milk is about 13 mEq per liter. Since oral potassium

becomes part of the body potassium pool, as long as body potassium is not excessive, the contribution

of potassium chloride supplementation should have little or no effect on the level in human milk.

PEDIATRIC USE

Clinical trial data from published literature have demonstrated the safety and effectiveness of potassium

chloride in children with diarrhea and malnutrition from birth to 18 years.

GERIATRIC USE

Clinical studies of potassium chloride did not include sufficient numbers of subjects aged 65 and over

to determine whether they respond differently from younger subjects. Other reported clinical

experience has not identified differences in responses between the elderly and younger patients. In

general, dose selection for an elderly patient should be cautious, usually starting at the low end of the

dosing range, reflecting the greater frequency of decreased hepatic, renal, or cardiac function, and of

concomitant disease or other drug therapy.

This drug is known to be substantially excreted by the kidney, and the risk of toxic reactions to this drug

may be greater in patients with impaired renal function. Because elderly patients are more likely to have

decreased renal function, care should be taken in dose selection, and it may be useful to monitor renal

function.

ADVERSE REACTIONS:

The following adverse reactions have been identified with use of oral potassium salts. Because these

reactions are reported voluntarily from a population of uncertain size, it is not always possible to

reliably estimate their frequency or establish a causal relationship to drug exposure.

The most common adverse reactions to oral potassium salts are nausea, vomiting, flatulence, abdominal

pain/discomfort, and diarrhea.

There have been reports of hyperkalemia and of upper and lower gastrointestinal conditions including,

obstruction, bleeding, ulceration, and perforation.

Skin rash has been reported rarely.

To report SUSPECTED ADVERSE REACTIONS contact AvKARE, Inc. at 1-855-361-3993; email drugsafety@avkare.com; or FDA at 1-800-FDA-1088 or www.fda.gov/medwatch.

OVERDOSAGE:

10.1 Symptoms

The administration of oral potassium salts to persons with normal excretory mechanisms for potassium

rarely causes serious hyperkalemia. However, if excretory mechanisms are impaired, potentially fatal

hyperkalemia can result.

Hyperkalemia is usually asymptomatic and may be manifested only by an increased serum potassium

concentration (6.5 to 8.0 mEq/L) and characteristic electrocardiographic changes (peaking of T-waves,

loss of P-waves, depression of S-T segment, and prolongation of the QT-interval). Late manifestations

include muscle paralysis and cardiovascular collapse from cardiac arrest (9 to 12 mEq/L).

10.2 Treatment

Treatment measures for hyperkalemia include the following:

1. Monitor closely for arrhythmias and electrolyte changes.

2. Eliminate foods and medications containing potassium and any agents with potassium-sparing

properties such as potassium-sparing diuretics, ARBs, ACE inhibitors, NSAIDs, certain nutritional

supplements, and many others.

3. Administer intravenous calcium gluconate if the patient is at no risk or low risk of developing

digitalis toxicity.

4. Administer 300 to 500 mL/hr of 10% dextrose solution containing 10 to 20 units of crystalline

insulin per 1,000 mL.

5. Correct acidosis, if present, with intravenous sodium bicarbonate.

6. Use exchange resins, hemodialysis, or peritoneal dialysis.

In patients who have been stabilized on digitalis, too rapid a lowering of the serum potassium

concentration can produce digitalis toxicity.

The extended-release feature means that absorption and toxic effects may be delayed for hours.

Consider standard measures to remove any unabsorbed drug.

DOSAGE AND ADMINISTRATION:

2.1 Adminis tration and Monitoring

If serum potassium concentration is <2.5 mEq/L, use intravenous potassium instead of oral

supplementation.

Monitoring

Monitor serum potassium and adjust dosages accordingly. Monitor serum potassium periodically during

maintenance therapy to ensure potassium remains in desired range.

The treatment of potassium depletion, particularly in the presence of cardiac disease, renal disease, or

acidosis requires careful attention to acid-base balance, volume status, electrolytes, including

Sections or subsections omitted from the full prescribing information are not listed.

magnesium, sodium, chloride, phosphate, and calcium, electrocardiograms and the clinical status of the

patient. Correct volume status, acid-base balance and electrolyte deficits as appropriate.

Administration

Take with meals and with a full glass of water or other liquid. Do not take on an empty stomach because

of the potential for gastric irritation [see Warnings and Precautions (5.1)].

Patients who have difficulty swallowing capsules may sprinkle the contents of the capsule onto a

spoonful of soft food. The soft food, such as applesauce or pudding, should be swallowed immediately

without chewing and followed with a glass of water or juice to ensure complete swallowing of the

microcapsules. Do not added to hot foods. Any microcapsule/food mixture should be used immediately

and not stored for future use.

2.2 Adult Dos ing

Dosage must be adjusted to the individual needs of each patient. Dosages greater than 40 mEq per day

should be divided such that no more than 40 mEq is given in a single dose.

Treatment of hypokalemia:Typical dose range is 40 to 100 mEq per day.

Maintenance or Prophylaxis:Typical dose is 20 mEq per day.

2.3 Pediatric Dos ing

Pediatric patients aged birth to 16 years old: Dosage must be adjusted to the individual needs of each

patient. Do not exceed as a single dose 1 mEq/kg or 20 mEq, whichever is lower.

Treatment of hypokalemia: The recommended initial dose is 2 to 4 mEq/kg/day in divided doses. If

deficits are severe or ongoing losses are great, consider intravenous therapy.

Maintenance or Prophylaxis: Typical dose is 1 mEq/kg/day.

HOW SUPPLIED:

Potassium Chloride Extended-release Capsules, USP, 8 mEq are white opaque capsules, imprinted with Andrx logo on the cap and 559 on the body, each containing 600mg microencapsulated potassium chloride (equivalent to 8 mEq K) in bottles of 90 (NDC 42291-678-90).

Potassium Chloride Extended-release Capsules, USP, 10 mEq are dark blue opaque capsules, imprinted with Andrx logo on the cap and 560 on the body, each containing 750 mg microencapsulated potassium chloride (equivalent to 10 mEq K) in bottles of 90 (42291-679-90), bottles of 500 (42291-679-50).

Store at 20° to 25°C (68° to 77°F) [See USP Controlled Room Temperature].

Dispense in a tight container as defined in the USP.

Manufactured for:
AvKARE, Inc.
Pulaski, TN 38478

Mfg. Rev. 02/15
AV Rev. 03/16 (P)